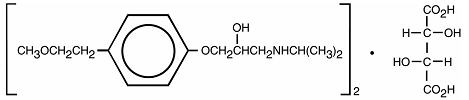 DRUG LABEL: Unknown
Manufacturer: Watson laboratories, Inc.
Category: prescription | Type: HUMAN PRESCRIPTION DRUG LABELING
Date: 20060407

METOPROLOL TARTRATE INJECTION USP
Rx only

DESCRIPTION

Metoprolol tartrate injection is a sterile solution containing metoprolol tartrate, a selective beta1-adrenoreceptor blocking agent, available for intravenous administration. Metoprolol tartrate is 1-(isopropylamino)-3-[p-(2-methoxyethyl)phenoxy]-2-propanol (2:1) dextro-tartrate salt. Its structural formula is:

(C15H25NO3)2 -C4H6O6

Metoprolol tartrate is a white, crystalline powder with a molecular weight of 684.82. It is very soluble in water; freely soluble in methylene chloride, in chloroform, and in alcohol; slightly soluble in acetone; and insoluble in ether.

Each 5 mL vial contains: Metoprolol Tartrate 5 mg, Sodium Chloride 45 mg, in Water for Injection q. s.

CLINICAL PHARMACOLOGY

Metoprolol tartrate is a beta-adrenergic receptor blocking agent. In vitro and in vivo animal studies have shown that it has a preferential effect on beta1 adrenoreceptors, chiefly located in cardiac muscle. This preferential effect is not absolute, however, and at higher doses, metoprolol also inhibits beta2 adrenoreceptors, chiefly located in the bronchial and vascular musculature.

Clinical pharmacology studies have confirmed the beta-blocking activity of metoprolol in man, as shown by (1) reduction in heart rate and cardiac output at rest and upon exercise, (2) reduction of systolic blood pressure upon exercise, (3) inhibition of isoproterenol-induced tachycardia, and (4) reduction of reflex orthostatic tachycardia.

Relative beta1 selectivity has been confirmed by the following: (1) In normal subjects, metoprolol is unable to reverse the beta2-mediated vasodilating effects of epinephrine. This contrasts with the effect of nonselective (beta1 plus beta2) beta blockers, which completely reverse the vasodilating effects of epinephrine. (2) In asthmatic patients, metoprolol reduces FEV1 and FVC significantly less than a nonselective beta blocker, propranolol, at equivalent beta1-receptor blocking doses.

Metoprolol has no intrinsic sympathomimetic activity, and membrane-stabilizing activity is detectable only at doses much greater than required for beta blockade. Metoprolol crosses the blood-brain barrier and has been reported in the CSF in a concentration 78% of the simultaneous plasma concentration. Animal and human experiments indicate that metoprolol slows the sinus rate and decreases AV nodal conduction.

In a large (1,395 patients randomized), double-blind, placebo-controlled clinical study, metoprolol was shown to reduce 3-month mortality by 36% in patients with suspected or definite myocardial infarction.

Patients were randomized and treated as soon as possible after their arrival in the hospital, once their clinical condition had stabilized and their hemodynamic status had been carefully evaluated.

Subjects were ineligible if they had hypotension, bradycardia, peripheral signs of shock, and/or more than minimal basal rales as signs of congestive heart failure. Initial treatment consisted of intravenous followed by oral administration of metoprolol tartrate or placebo, given in a coronary care or comparable unit. Oral maintenance therapy with metoprolol or placebo was then continued for 3 months. After this double-blind period, all patients were given metoprolol and followed up to 1 year.

The median delay from the onset of symptoms to the initiation of therapy was 8 hours in both the metoprolol and placebo treatment groups. Among patients treated with metoprolol, there were comparable reductions in 3-month mortality for those treated early (≤ 8 hours) and those in whom treatment was started later. Significant reductions in the incidence of ventricular fibrillation and in chest pain following initial intravenous therapy were also observed with metoprolol and were independent of the interval between onset of symptoms and initiation of therapy.

The precise mechanism of action of metoprolol in patients with suspected or definite myocardial infarction is not known.

In this study, patients treated with metoprolol received the drug both very early (intravenously) and during a subsequent 3-month period, while placebo patients received no beta blocker treatment for this period. The study thus was able to show a benefit from the overall metoprolol regimen but cannot separate the benefit of very early intravenous treatment from the benefit of later beta blocker therapy. Nonetheless, because the overall regimen showed a clear beneficial effect on survival without evidence of an early adverse effect on survival, one acceptable dosage regimen is the precise regimen used in the trial. Because the specific benefit of very early treatment remains to be defined however, it is also reasonable to administer the drug orally to patients at a later time as is recommended for certain other beta blockers.

Pharmacokinetics

In man, absorption of metoprolol is rapid and complete. Plasma levels following oral administration, however, approximate 50% of levels following intravenous administration, indicating about 50% first-pass metabolism.

Plasma levels achieved are highly variable after oral administration. Only a small fraction of the drug (about 12%) is bound to human serum albumin. Elimination is mainly by biotransformation in the liver, and the plasma half-life ranges from approximately 3 to 7 hours. The systemic availability and half-life of metoprolol in patients with renal failure do not differ to a clinically significant degree from those in normal subjects. Consequently, no reduction in dosage is usually needed in patients with chronic renal failure.

Following intravenous administration of metoprolol, the urinary recovery of unchanged drug is approximately 10%. When the drug was infused over a 10 minute period, in normal volunteers, maximum beta blockade was achieved at approximately 20 minutes. Doses of 5 mg and 15 mg yielded a maximal reduction in exercise-induced heart rate of approximately 10% and 15%, respectively. The effect on exercise heart rate decreased linearly with time at the same rate for both doses, and disappeared at approximately 5 hours and 8 hours for the 5 mg and 15 mg doses, respectively.

Equivalent maximal beta-blocking effect is achieved with oral and intravenous doses in the ratio of approximately 2.5:1.

There is a linear relationship between the log of plasma levels and reduction of exercise heart rate.

In several studies of patients with acute myocardial infarction, intravenous followed by oral administration of metoprolol caused a reduction in heart rate, systolic blood pressure, and cardiac output. Stroke volume, diastolic blood pressure, and pulmonary artery end diastolic pressure remained unchanged.

INDICATIONS AND USAGE

Myocardial Infarction

Metoprolol tartrate injection and tablets are indicated in the treatment of hemodynamically stable patients with definite or suspected acute myocardial infarction to reduce cardiovascular mortality. Treatment with intravenous metoprolol tartrate can be initiated as soon as the patient’s clinical condition allows (see DOSAGE AND ADMINISTRATION, CONTRAINDICATIONS, and WARNINGS). Alternatively, treatment can begin within 3 to 10 days of the acute event (see DOSAGE AND ADMINISTRATION).

CONTRAINDICATIONS

Myocardial Infarction

Metoprolol is contraindicated in patients with a heart rate < 45 beats/min; second- and third-degree heart block; significant first-degree heart block (P-R interval ≥ 0.24 sec); systolic blood pressure < 100 mmHg; or moderate-to-severe cardiac failure (see WARNINGS).

WARNINGS

Myocardial Infarction

Cardiac Failure:

Sympathetic stimulation is a vital component supporting circulatory function, and beta blockade carries the potential hazard of depressing myocardial contractility and precipitating or exacerbating minimal cardiac failure.

During treatment with metoprolol, the hemodynamic status of the patient should be carefully monitored. If heart failure occurs or persists despite appropriate treatment, metoprolol should be discontinued.

Bradycardia:

Metoprolol produces a decrease in sinus heart rate in most patients; this decrease is greatest among patients with high initial heart rates and least among patients with low initial heart rates. Acute myocardial infarction (particularly inferior infarction) may in itself produce significant lowering of the sinus rate. If the sinus rate decreases to < 40 beats/min, particularly if associated with evidence of lowered cardiac output, atropine (0.25-0.5 mg) should be administered intravenously. If treatment with atropine is not successful, metoprolol should be discontinued, and cautious administration of isoproterenol or installation of a cardiac pacemaker should be considered.

AV Block:

Metoprolol slows AV conduction and may produce significant first-(P-R interval ≥0.26 sec), second-, or third-degree heart block. Acute myocardial infarction also produces heart block.

If heart block occurs, metoprolol should be discontinued and atropine (0.25-0.5 mg) should be administered intravenously. If treatment with atropine is not successful, cautious administration of isoproterenol or installation of a cardiac pacemaker should be considered.

Hypotension:

If hypotension (systolic blood pressure ≤90 mmHg) occurs, metoprolol should be discontinued, and the hemodynamic status of the patient and the extent of myocardial damage carefully assessed. Invasive monitoring of central venous, pulmonary capillary wedge, and arterial pressures may be required. Appropriate therapy with fluids, positive inotropic agents, balloon counterpulsation, or other treatment modalities should be instituted. If hypotension is associated with sinus bradycardia or AV block, treatment should be directed at reversing these (see above).

Bronchospastic Diseases:

PATIENTS WITH BRONCHOSPASTIC DISEASES SHOULD, IN GENERAL, NOT RECEIVE BETA BLOCKERS. Because of its relative beta1 selectivity, metoprolol may be used with extreme caution in patients with bronchospastic disease. Because it is unknown to what extent beta2-stimulating agents may exacerbate myocardial ischemia and the extent of infarction, these agents should not be used prophylactically. If bronchospasm not related to congestive heart failure occurs, metoprolol should be discontinued. A theophylline derivative or a beta2 agonist may be administered cautiously, depending on the clinical condition of the patient. Both theophylline derivatives and beta2 agonists may produce serious cardiac arrhythmias.

PRECAUTIONS

General

Metoprolol should be used with caution in patients with impaired hepatic function.

Laboratory Tests

Clinical laboratory findings may include elevated levels of serum transaminase, alkaline phosphatase, and lactate dehydrogenase.

Drug Interactions

Catecholamine-depleting drugs (e.g., reserpine) may have an additive effect when given with beta-blocking agents. Patients treated with metoprolol plus a catecholamine depletor should therefore be closely observed for evidence of hypotension or marked bradycardia, which may produce vertigo, syncope, or postural hypotension.

While taking beta blockers, patients with a history of severe anaphylactic reaction to a variety of allergens may be more reactive to repeated challenge, either accidental, diagnostic or therapeutic. Such patients may be unresponsive to the usual doses of epinephrine used to treat allergic reaction.

Carcinogenesis, Mutagenesis, Impairment of Fertility

Long-term studies in animals have been conducted to evaluate carcinogenic potential. In a 2-year study in rats at three oral dosage levels of up to 800 mg/kg per day, there was no increase in the development of spontaneously occurring benign or malignant neoplasms of any type. The only histologic changes that appeared to be drug related were an increased incidence of generally mild focal accumulation of foamy macrophages in pulmonary alveoli and a slight increase in biliary hyperplasia. In a 21-month study in Swiss albino mice at three oral dosage levels of up to 750 mg/kg per day, benign lung tumors (small adenomas) occurred more frequently in female mice receiving the highest dose than in untreated control animals. There was no increase in malignant or total (benign plus malignant) lung tumors, nor in the overall incidence of tumors or malignant tumors. This 21-month study was repeated in CD-1 mice, and no statistically or biologically significant differences were observed between treated and control mice of either sex for any type of tumor.

All mutagenicity tests performed (a dominant lethal study in mice, chromosome studies in somatic cells, a Salmonella/mammalian-microsome mutagenicity test, and a nucleus anomaly test in somatic interphase nuclei) were negative.

No evidence of impaired fertility due to metoprolol was observed in a study performed in rats at doses up to 55.5 times the maximum daily human dose of 450 mg.

Pregnancy Category C

Metoprolol has been shown to increase postimplantation loss and decrease neonatal survival in rats at doses up to 55.5 times the maximum daily human dose of 450 mg. Distribution studies in mice confirm exposure of the fetus when metoprolol is administered to the pregnant animal. These studies have revealed no evidence of impaired fertility or teratogenicity. There are no adequate and well-controlled studies in pregnant women. Because animal reproduction studies are not always predictive of human response, this drug should be used during pregnancy only if clearly needed.

Nursing Mothers

Metoprolol is excreted in breast milk in very small quantity. An infant consuming 1 liter of breast milk daily would receive a dose of less than 1 mg of the drug. Caution should be exercised when metoprolol is administered to a nursing woman.

Pediatric Use

Safety and effectiveness in children have not been established.

ADVERSE REACTIONS

Myocardial Infarction

Central Nervous System:

Tiredness has been reported in about 1 of 100 patients. Vertigo, sleep disturbances, hallucinations, headache, dizziness, visual disturbances, confusion, and reduced libido have also been reported, but a drug relationship is not clear.

Cardiovascular:

In the randomized comparison of metoprolol and placebo described in the CLINICAL PHARMACOLOGY section, the following adverse reactions were reported:

 |  |  | Metoprolol | Placebo
Hypotension |  |  | 27.4% | 23.2%
 | (systolic BP < 90 mmHg)
Bradycardia |  |  | 15.9% | 6.7%
 | (heart rate < 40 beats/min)
Second- or third-degree heart block |  |  | 4.7% | 4.7%
First-degree heart block |  |  | 5.3% | 1.9%
 | (P-R ≥ 0.26 sec)
Heart failure |  |  | 27.5% | 29.6%

Respiratory:

Dyspnea of pulmonary origin has been reported in fewer than 1 of 100 patients.

Gastrointestinal:

Nausea and abdominal pain have been reported in fewer than 1 of 100 patients.

Dermatologic:

Rash and worsened psoriasis have been reported, but a drug relationship is not clear.

Miscellaneous:

Unstable diabetes and claudication have been reported, but a drug relationship is not clear.

Potential Adverse Reactions

A variety of adverse reactions not listed above have been reported with other beta-adrenergic blocking agents and should be considered potential adverse reactions to metoprolol.

Central Nervous System:

Reversible mental depression progressing to catatonia; an acute reversible syndrome characterized by disorientation for time and place, short-term memory loss, emotional lability, slightly clouded sensorium, and decreased performance on neuropsychometrics.

Cardiovascular:

Intensification of AV block (see CONTRAINDICATIONS).

Hematologic:

Agranulocytosis, nonthrombocytopenic purpura, thrombocytopenic purpura.

Hypersensitive Reactions:

Fever combined with aching and sore throat, laryngospasm, and respiratory distress.

OVERDOSAGE

Acute Toxicity

Several cases of overdosage have been reported, some leading to death.

Oral LD50’s (mg/kg): mice, 1158-2460; rats, 3090-4670.

Signs and Symptoms

Potential signs and symptoms associated with overdosage with metoprolol are bradycardia, hypotension, bronchospasm, and cardiac failure.

Treatment

There is no specific antidote.

In general, patients with acute or recent myocardial infarction may be more hemo-dynamically unstable than other patients and should be treated accordingly (see WARNINGS, Myocardial Infarction).

On the basis of the pharmacologic actions of metoprolol, the following general measures should be employed:

Elimination of the Drug:

Gastric lavage should be performed.

Bradycardia:

Atropine should be administered. If there is no response to vagal blockade, isoproterenol should be administered cautiously.

Hypotension:

A vasopressor should be administered, e.g., norepinephrine or dopamine.

Bronchospasm:

A beta2-stimulating agent and/or a theophylline derivative should be administered.

Cardiac Failure: A digitalis glycoside and diuretic should be administered. In shock resulting from inadequate cardiac contractility, administration of dobutamine, isoproterenol, or glucagon may be considered.

DOSAGE AND ADMINISTRATION

Myocardial Infarction

Early Treatment:

During the early phase of definite or suspected acute myocardial infarction, treatment with metoprolol tartrate can be initiated as soon as possible after the patient’s arrival in the hospital. Such treatment should be initiated in a coronary care or similar unit immediately after the patient’s hemodynamic condition has stabilized.

Treatment in this early phase should begin with the intravenous administration of three bolus injections of 5 mg of metoprolol tartrate each; the injections should be given at approximately 2-minute intervals. During the intravenous administration of metoprolol, blood pressure, heart rate, and electrocardiogram should be carefully monitored.

In patients who tolerate the full intravenous dose (15 mg), metoprolol tartrate tablets, 50 mg every 6 hours, should be initiated 15 minutes after the last intravenous dose and continued for 48 hours. Thereafter, patients should receive a maintenance dosage of 100 mg twice daily (see Late Treatment below).

Patients who appear not to tolerate the full intravenous dose should be started on metoprolol tartrate tablets either 25 mg or 50 mg every 6 hours (depending on the degree of intolerance) 15 minutes after the last intravenous dose or as soon as their clinical condition allows. In patients with severe intolerance, treatment with metoprolol should be discontinued (see WARNINGS).

Late Treatment:

Patients with contraindications to treatment during the early phase of suspected or definite myocardial infarction, patients who appear not to tolerate the full early treatment, and patients in whom the physician wishes to delay therapy for any other reason should be started on metoprolol tartrate tablets, 100 mg twice daily, as soon as their clinical condition allows. Therapy should be continued for at least 3 months. Although the efficacy of metoprolol beyond 3 months has not been conclusively established, data from studies with other beta blockers suggest that treatment should be continued for 1 to 3 years.

NOTE: Parenteral drug products should be inspected visually for particulate matter and discoloration prior to administration, whenever solution and container permit.

HOW SUPPLIED

Metoprolol Tartrate Injection USP, 1 mg/mL is available in 5 mL single dose vials, in cartons of 3.

Store at controlled room temperature 15°-30°C (59°-86°F).

PROTECT FROM LIGHT. Store in carton until time of use.

Literature revised: December 2002
Product No.: 0958-05

695309580591*A1

Watson Laboratories, Inc.
Corona, CA 92880 USA